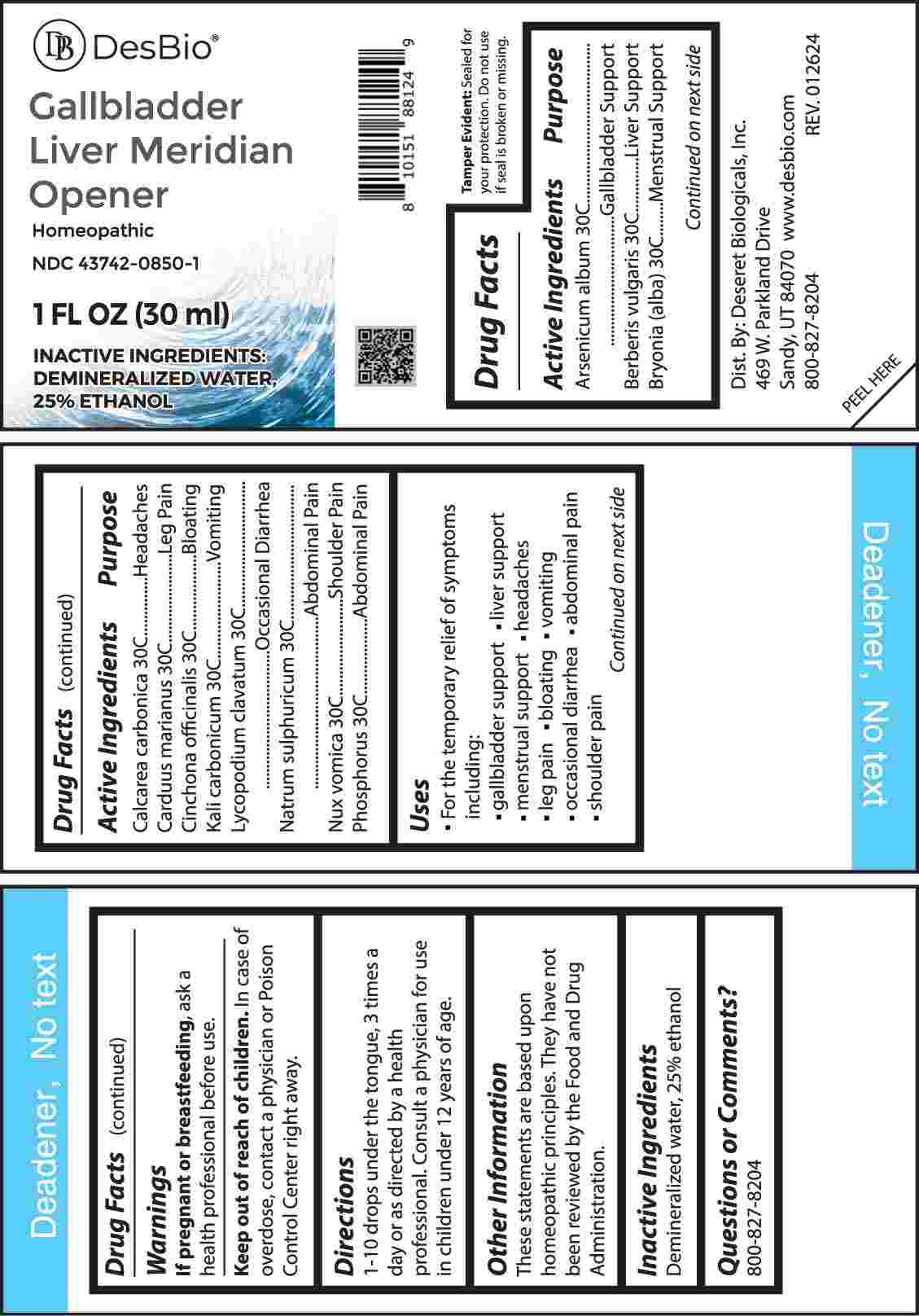 DRUG LABEL: Gallbladder Liver Meridian Opener
NDC: 43742-0850 | Form: LIQUID
Manufacturer: Deseret Biologicals, Inc.
Category: homeopathic | Type: HUMAN OTC DRUG LABEL
Date: 20240430

ACTIVE INGREDIENTS: ARSENIC TRIOXIDE 30 [hp_C]/1 mL; BERBERIS VULGARIS ROOT BARK 30 [hp_C]/1 mL; BRYONIA ALBA ROOT 30 [hp_C]/1 mL; OYSTER SHELL CALCIUM CARBONATE, CRUDE 30 [hp_C]/1 mL; MILK THISTLE 30 [hp_C]/1 mL; CINCHONA OFFICINALIS BARK 30 [hp_C]/1 mL; POTASSIUM CARBONATE 30 [hp_C]/1 mL; LYCOPODIUM CLAVATUM SPORE 30 [hp_C]/1 mL; SODIUM SULFATE 30 [hp_C]/1 mL; STRYCHNOS NUX-VOMICA SEED 30 [hp_C]/1 mL; PHOSPHORUS 30 [hp_C]/1 mL
INACTIVE INGREDIENTS: WATER; ALCOHOL

DRUG FACTS:

ACTIVE INGREDIENTS:

Arsenicum Album 30C, Berberis Vulgaris 30C, Bryonia (Alba) 30C, Calcarea Carbonica 30C, Carduus Marianus 30C, Cinchona Officinalis 30C, Kali Carbonicum 30C, Lycopodium Clavatum 30C, Natrum Sulphuricum 30C, Nux Vomica 30C, Phosphorus 30C.

PURPOSE:

Arsenicum Album – Gallbladder Support, Berberis Vulgaris – Liver Support, Bryonia (Alba) – Menstrual Support, Calcarea Carbonica - Headaches, Carduus Marianus – Leg Pain, Cinchona Officinalis - Bloating, Kali Carbonicum - Vomiting, Lycopodium Clavatum – Occasional Diarrhea, Natrum Sulphuricum – Abdominal Pain, Nux Vomica – Shoulder Pain, Phosphorus – Abdominal Pain

USES:

• For the temporary relief of symptoms including:

• gallbladder support • liver support • menstrual support • headaches • leg pain

• bloating • vomiting • occasional diarrhea • abdominal pain • shoulder pain

These statements are based upon homeopathic principles. They have not been reviewed by the Food and Drug Administration.

WARNINGS:

If pregnant or breast-feeding, ask a health professional before use.

Keep out of reach of children. In case of overdose, contact a physician or Poison Control Center right away.

Tamper Evident: Sealed for your protection. Do not use if seal is broken or missing.

KEEP OUT OF REACH OF CHILDREN:

In case of overdose, contact a physician or Poison Control Center right away.

DIRECTIONS:

1-10 drops under the tongue, 3 times a day or as directed by a health professional. Consult a physician for use in children under 12 years of age.

INACTIVE INGREDIENTS:

Demineralized water, 25% ethanol

QUESTIONS:

Dist. By: Deseret Biologicals, Inc.
469 W. Parkland Drive
Sandy, UT 84070

www.desbio.com

800-827-8204

PACKAGE LABEL DISPLAY:

Des Bio

Gallbladder Liver

Meridian Opener

Homeopathic

NDC 43742-0850-1

1 FL OZ (30 ml)